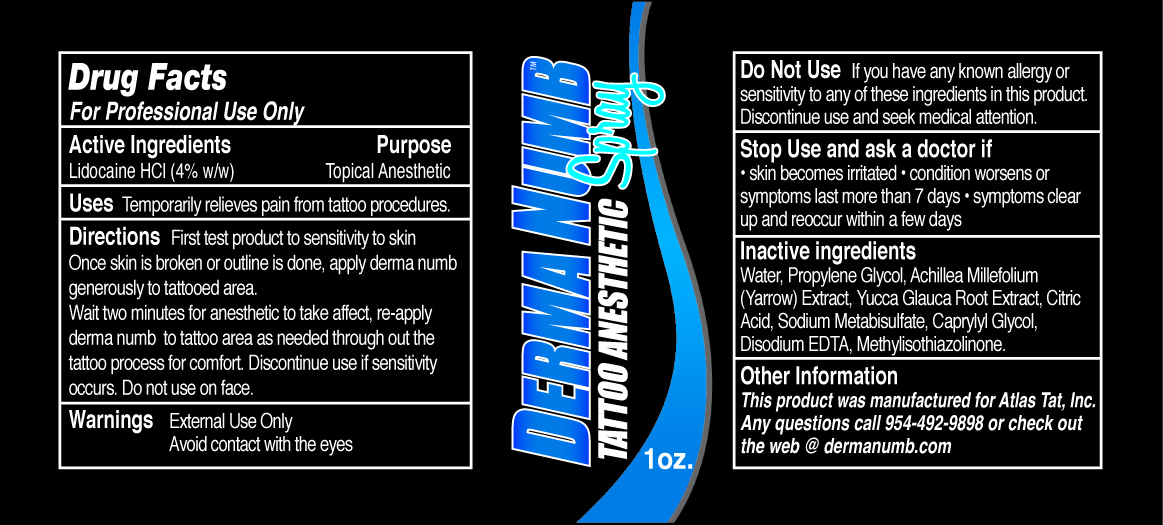 DRUG LABEL: Derma Numb
NDC: 53200-001 | Form: SPRAY
Manufacturer: Atlas Tat Inc.
Category: prescription | Type: HUMAN PRESCRIPTION DRUG LABEL
Date: 20121003

ACTIVE INGREDIENTS: LIDOCAINE HYDROCHLORIDE 40 mg/1 g
INACTIVE INGREDIENTS: WATER; SODIUM METABISULFITE; PROPYLENE GLYCOL; EDETATE DISODIUM; ACHILLEA MILLEFOLIUM; YUCCA GLAUCA ROOT; DIAZOLIDINYL UREA

Derma Numb Tattoo Anesthetic Spray

Active Ingredients

Lidocaine HCI

Purpose

Topical Anesthetic

Uses

Temporarily relieves pain from tattoo procedures.

Directions

First test product to sensitivity to skin.

Once skin is broken or outline is done, apply derma numb generously to tattooed area.

Wait two minutes for anesthetic to take affect, re-apply derma numb to tattoo area as needed through out the tattoo process for comfort. Discontinue use if sensitivity occurs. Do not use on face.

Warnings

External Use Only

Avoid contact with the eyes

Do Not Use

If you have any known allergy or sensitivity to any of these ingredients in this product. Discontinue use and seek medical attention.

Stop Use and ask a doctor if

• skin becomes irritated • condition worsens or symptoms last more than7 days • symptoms clear up and reoccur with a few days

Inactive ingredients

Water, Propylene Glycol, Achillea Millefolium (Yarrow) Extract, Yucca Glauca Root Extract, Citric Acid, Sodium Metabisulfate, Caprylyl Glycol, Disodium EDTA, Methylisothiazolinone.

Other Information

This product was manufactured for Atlas Tat, Inc.

Any questions call 954-492-9898 or check out the web @ dermnumb.com